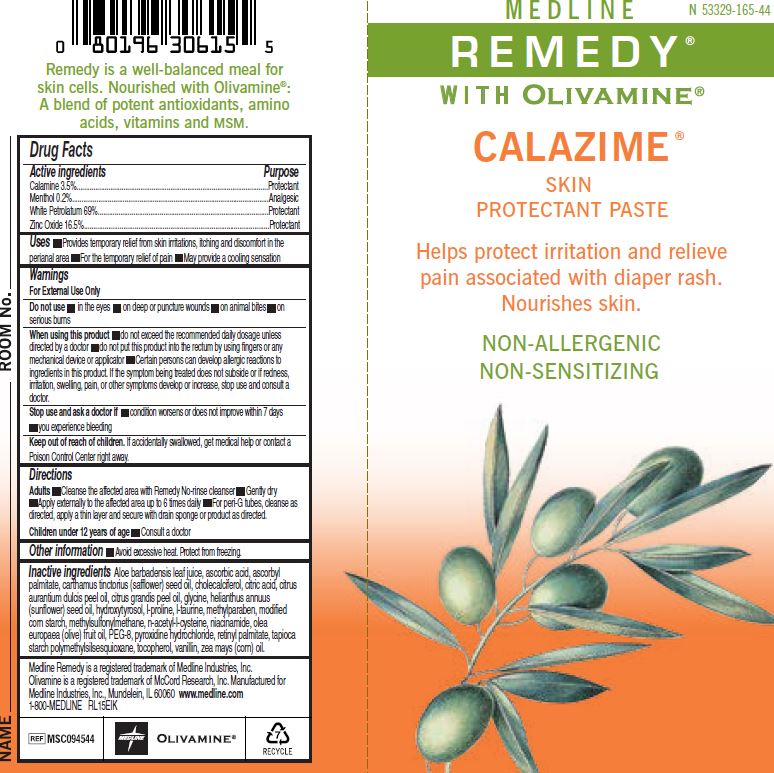 DRUG LABEL: REMEDY Calazime Skin Protectant
NDC: 53329-165 | Form: PASTE
Manufacturer: Medline Industries, LP
Category: otc | Type: HUMAN OTC DRUG LABEL
Date: 20250129

ACTIVE INGREDIENTS: FERRIC OXIDE RED 0.5 g/100 g; MENTHOL 0.2 g/100 g; ZINC OXIDE 19.5 g/100 g; PETROLATUM 69 g/100 g
INACTIVE INGREDIENTS: ALOE VERA LEAF; ASCORBIC ACID; ASCORBYL PALMITATE; SAFFLOWER OIL; CHOLECALCIFEROL; CITRIC ACID MONOHYDRATE; ORANGE OIL; CITRUS MAXIMA FRUIT RIND OIL; GLYCINE; SUNFLOWER OIL; HYDROXYTYROSOL; METHYLPARABEN; MODIFIED CORN STARCH (1-OCTENYL SUCCINIC ANHYDRIDE); DIMETHYL SULFONE; ACETYLCYSTEINE; NIACINAMIDE; OLIVE OIL; POLYETHYLENE GLYCOL 400; PYRIDOXINE HYDROCHLORIDE; VITAMIN A PALMITATE; .ALPHA.-TOCOPHEROL; VANILLIN; CORN OIL

165 REMEDY Calazime Skin Protectant

Active ingredient

Calamine 3.5%

Menthol 0.2%

White Petrolatum 69%

Zinc Oxide 16.5%

Purpose

Protectant

Protectant

Prot

Protectant

Uses

- Provides temporary relief from skin irritations, itching and discomfort in the perianal area
- For the temporary relief of pain
- May provide a cooling sensation

Warnings

For External Use Only

Do not use

- in the eyes
- on deep or puncture wounds
- on animal bites
- on serious burns.

When using this product

- do not exceed the recommended daily dosage unless directed by a doctor
- do not put this product into the rectum by using fingers or any mechanical device or applicator
- Certain persons can develop allergic reactions to ingredients in this product. If the symptom being treated does not subside or if redness, irritation, swelling, pain, or other symptoms develop or increase, stop use and consult a doctor

Stop use and ask a doctor if

- condition worsens or does not improved within 7 days
- you experience bleeding

Keep out of reach of children.

- If accidentally swallowed, get medical help or contact a Poison Control Center right away.

Directions

Adults

- Cleanse the affected area with Remedy No-rinse cleanser
- Gently dry
- Apply externally to the affected area up to 6 times daily
- For peri-G tubes, cleanse as directed, apply thin layer and secure with drain sponge or product as directed.

Children under 12 years of age

- Consult a doctor

Other information

- Protect from freezing, Avoid excessive heat.

Inactive ingredients

Aloe Barbadensis Leaf Juice, Ascorbic Acid, Ascorbyl Palmitate, Carthamus Tinctorius (Safflower) Seed Oil, Cholecalciferol, Citric Acid, Citrus Aurantium Dulcis Peel Oil, Citrus Grandis Peel Oil, Glycine, Helianthus Annuus (Sunflower) Seed Oil, Hydroxytyrosol, L-proline, L-taurine, Methylparaben, Modified Corn Starch, Methylsulfonymethane, N-acetyl-L-cysteine, Niacinamide, Olea Europaea (Olive) Fruit Oil, PEG-8, Pyridoxine Hydrochloride, Retinyl Palmitate, Tapioca Starch Polymethylsilsesquioxane, Tocopherol, Vanillin, Zea Mays (Corn) Oil.

Medline Remedy is a registered trademark of Medline Industries, Inc.
Olivamine is a registered trademark of McCord Research, Inc. Manufactured for
Medline Industries, Inc., Mundelein, IL 60060 www.medline.com
1-800-MEDLINE